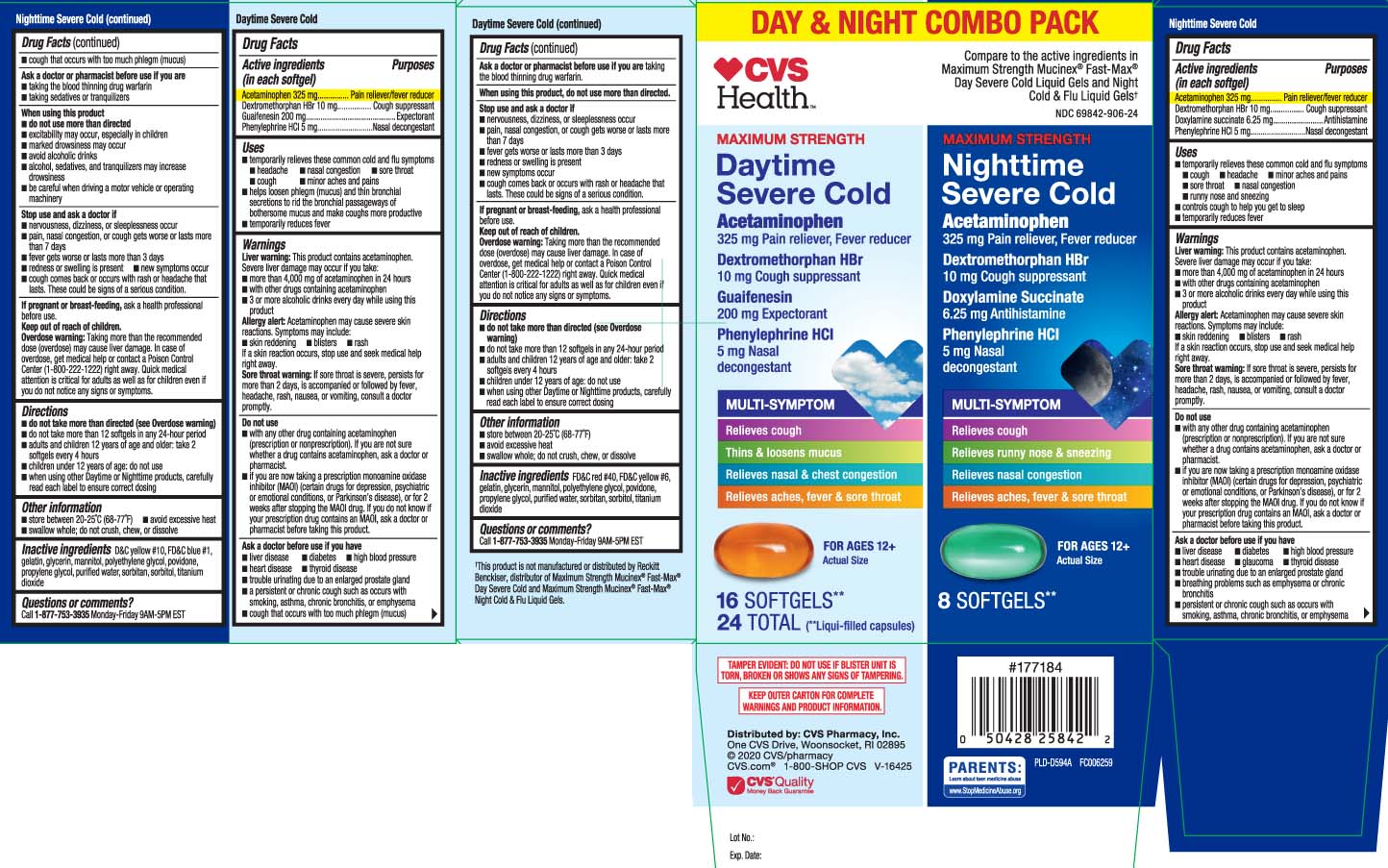 DRUG LABEL: Daytime Mucus Relief Severe Cold and Nighttime Cold and Flu
NDC: 69842-906 | Form: KIT | Route: ORAL
Manufacturer: CVS Pharmacy
Category: otc | Type: HUMAN OTC DRUG LABEL
Date: 20250818

ACTIVE INGREDIENTS: ACETAMINOPHEN 325 mg/1 1; DEXTROMETHORPHAN HYDROBROMIDE 10 mg/1 1; DOXYLAMINE SUCCINATE 6.25 mg/1 1; PHENYLEPHRINE HYDROCHLORIDE 5 mg/1 1; ACETAMINOPHEN 325 mg/1 1; DEXTROMETHORPHAN HYDROBROMIDE 10 mg/1 1; GUAIFENESIN 200 mg/1 1; PHENYLEPHRINE HYDROCHLORIDE 5 mg/1 1
INACTIVE INGREDIENTS: D&C YELLOW NO. 10; FD&C BLUE NO. 1; GELATIN; GLYCERIN; POLYETHYLENE GLYCOL, UNSPECIFIED; POVIDONE; PROPYLENE GLYCOL; WATER; SORBITAN; SORBITOL; MANNITOL; TITANIUM DIOXIDE; FD&C RED NO. 40; FD&C YELLOW NO. 6; GELATIN; GLYCERIN; POLYETHYLENE GLYCOL, UNSPECIFIED; POVIDONE; PROPYLENE GLYCOL; WATER; SORBITAN; SORBITOL; TITANIUM DIOXIDE; MANNITOL

Drug Facts

Active ingredients in Daytime (in each softgel)

Acetaminophen 325 mg

Dextromethorphan HBr 10 mg

Guaifenesin 200 mg

Phenylephrine HCl 5 mg

Active ingredients in Nighttime (in each softgel)

Acetaminophen 325 mg

Dextromethorphan HBr 10 mg

Doxylamine succinate 6.25 mg

Phenylephrine HCI 5 mg

Purpose for Daytime

Pain reliever/fever reducer

Cough suppressant

Expectorant

Nasal decongestant

Purpose for Nighttime

Pain reliever/fever reducer

Cough suppressant

Antihistamine

Nasal decongestant

Uses

DAYTIME

- temporarily relieves these common cold and flu symptoms
  - headache
  - nasal congestion
  - sore throat
  - cough
  - minor aches and pains
  - helps loosen phlegm (mucus) and thin bronchial secretions to rid the bronchial passageways of bothersome mucus and make coughs more productive
  - temporarily reduces fever

NIGHTTIME

- temporarily relieves these common cold and flu symptoms
  - cough
  - headache
  - minor aches and pains
  - sore throat
  - nasal congestion
  - runny nose and sneezing
  - controls cough to help you get to sleep
  - temporarily reduces fever

Warnings

DAYTIME and NIGHTTIME

Liver warning: These products contain acetaminophen. Severe liver damage may occur if you take:

- more than 4,000 mg of acetaminophen in 24 hours
- with other drugs containing acetaminophen
- 3 or more alcoholic drinks every day while using this product

Allergy alert: Acetaminophen may cause severe skin reactions. Symptoms may include:

- skin reddening
- blisters
- rash

If a skin reaction occurs, stop use and seek medical help right away

Sore throat warning: If sore throat is severe, persists for more than 2 days, is accompanied or followed by fever, headache, rash, nausea, or vomiting, consult a doctor promptly.

Do not use

DAYTIME and NIGHTTIME

- with any other drug containing acetaminophen (prescription or nonprescription). If you are not sure whether a drug contains acetaminophen, ask a doctor or pharmacist.
- if you are now taking a prescription monoamine oxidase inhibitor (MAOI) (certain drugs for depression, psychiatric or emotional conditions, or Parkinson’s disease), or for 2 weeks after stopping the MAOI drug. If you do not know if your prescription drug contains an MAOI, ask a doctor or pharmacist before taking this product.

Ask a doctor before use if you have

DAYTIME

- liver disease
- diabetes
- high blood pressure
- heart disease
- thyroid disease
- trouble urinating due to an enlarged prostate gland
- a persistent or chronic cough such as occurs with smoking, asthma, chronic bronchitis, or emphysema
- cough that occurs with too much phlegm (mucus)

NIGHTTIME

- liver disease
- diabetes
- high blood pressure
- heart disease
- glaucoma
- thyroid disease
- trouble urinating due to an enlarged prostate gland
- a breathing problem or chronic cough that lasts or as occurs with smoking, asthma, chronic bronchitis, or emphysema
- cough that occurs with too much phlegm (mucus

Ask a doctor or pharmacist before use if you are

DAYTIME

taking the blood thinning drug warfarin

NIGHTTIME

taking the blood thinning drug warfarin

taking sedatives or tranquilizers

When using this product,

DAYTIME

do not use more than directed

NIGHTTIME

- do not use more than directed
- excitability may occur, especially in children
- marked drowsiness may occur
- avoid alcoholic drinks
- alcohol, sedatives, and tranquilizers may increase drowsiness
- be careful when driving a motor vehicle or operating machinery

Stop use and ask a doctor if

DAYTIME and NIGHTTIME

- nervousness, dizziness, or sleeplessness occur
- pain, nasal congestion, or cough gets worse or lasts more than 7 days
- fever gets worse or lasts more than 3 days
- redness or swelling is present
- new symptoms occur
- cough comes back or occurs with rash or headache that lasts. These coukld be signs of a serious condition.

If pregnant or breast-feeding,

DAYTIME and NIGHTTIME

ask a health professional before use.

Keep out of reach of children.

DAYTIME and NIGHTTIME

Overdose warning: Taking more than the recommended dose can cause liver damage. In case of overdose, get medical help or contact a Poison Control Center (1-800-222-1222) right away. Quick medical attention is critical for adults as well as for children even if you do not notice any signs or symptoms.

Directions

DAYTIME

- do not take more than directed (see Overdose warning)
- do not take more than 12 softgels (Daytime and NightTime) in any 24-hour period
- adults and children 12 years of age and older: take 2 softgels every 4 hours
- children under 12 years of age: do not use
- when using other Daytime or Nighttime products, carefully read each label to ensure correct dosing

NIGHTTIME

- do not take more than directed (see Overdose warning)
- do not take more than 12 softgels (Daytime and Nighttime) in any 24-hour period
- adults and children 12 years of age and older: take 2 softgels every 4 hours
- children under 12 years of age: do not use
- when using other Daytime or Nighttime products, carefully read each label to ensure correct dosing

Other information

DAYTIME and NIGHTTIME

- store between 20-25ºC (68-77ºF)
- avoid excessive heat
- swallow whole, do not crush, chew, or dissolve

Inactive ingredients

DAYTIME

FD&C red #40, FD&C yellow #6, gelatin, glycerin, mannitol, polyethylene glycol, povidone, propylene glycol, purified water, sorbitan, sorbitol, titanium dioxide

NIGHTTIME

D&C yellow #10, FD&C blue #1, gelatin, glycerin, mannitol, polyethylene glycol, povidone, propylene glycol, purified water, sorbitan, sorbitol, titanium dioxide

Questions or comments?

DAYTIME and NIGHTTIME

Call 1-877-753-3935 Monday-Friday 9AM-5PM EST

Principal Display Panel

DAY & NIGHT COMBO PACK

Compare to the active ingredients in Maximum Strength Mucinex® FAST-Max® Day Severe Cold Liquid Gels and Night Cold & Flu Liquid Gels†

DAYTIME

MAXIMUM STRENGTH

Daytime Severe Cold

Acetaminophen 325 mg Pain Reliever ; Fever Reducer

Dextromethorphan HBr 10 mg Cough Suppressant

Guaifenesin 200 mg Expectorant

Phenylephrine HCL - 5 mg Nasal Decongestant

MULTI-SYMPTOM

- Relieves cough
- Thins & loosens mucus
- Relieves nasal & chest congestion
- Relieves aches, fever & sore throat

FOR AGES 12+

SOFTGELS**

(Liqui-filled capsules)

NIGHTTIME

MAXIMUM STRENGTH

Nighttime Cold & Flu

Acetaminophen 325 mg Pain reliever, Fever reducer

Dextromethorphan HBr 10 mg Cough suppressant

Doxylamine Succinate 6.25 mg Antihistamine

Phenylephrine HCL 5 mg Nasal decongestant

MULTI-SYMPTOM

- Relieves cough
- Relieves runny nose & sneezing
- Relieves nasal congestion
- Relieves aches, fever & sore throat

FOR AGES 12+

SOFTGELS**

(*Liqui-Filled Capsules)

*This product is not manufactured or distributed by Reckitt Benckiser, distributor of Maximum Strength Mucinex® Fast-Max® Day Severe Cold and Maximum Strength Mucinex® Fast-Max® Night Cold & Flu Liquid Gels.

TAMPER EVIDENT: DO NOT USE IF BLISTER UNIT IS TORN, BROKEN OR SHOWS ANY SIGNS OF TAMPERING.

KEEP OUTER CARTON FOR COMPLETE WARNINGS AND PRODUCT INFORMATION.

Distributed by: CVS Pharmacy, Inc.

One CVS Drive, Woonsocket, RI 02895

Product Label

CVS HEALTH Maximum Strength Daytime Severe Cold, Maximum Strength Nighttime Severe Cold